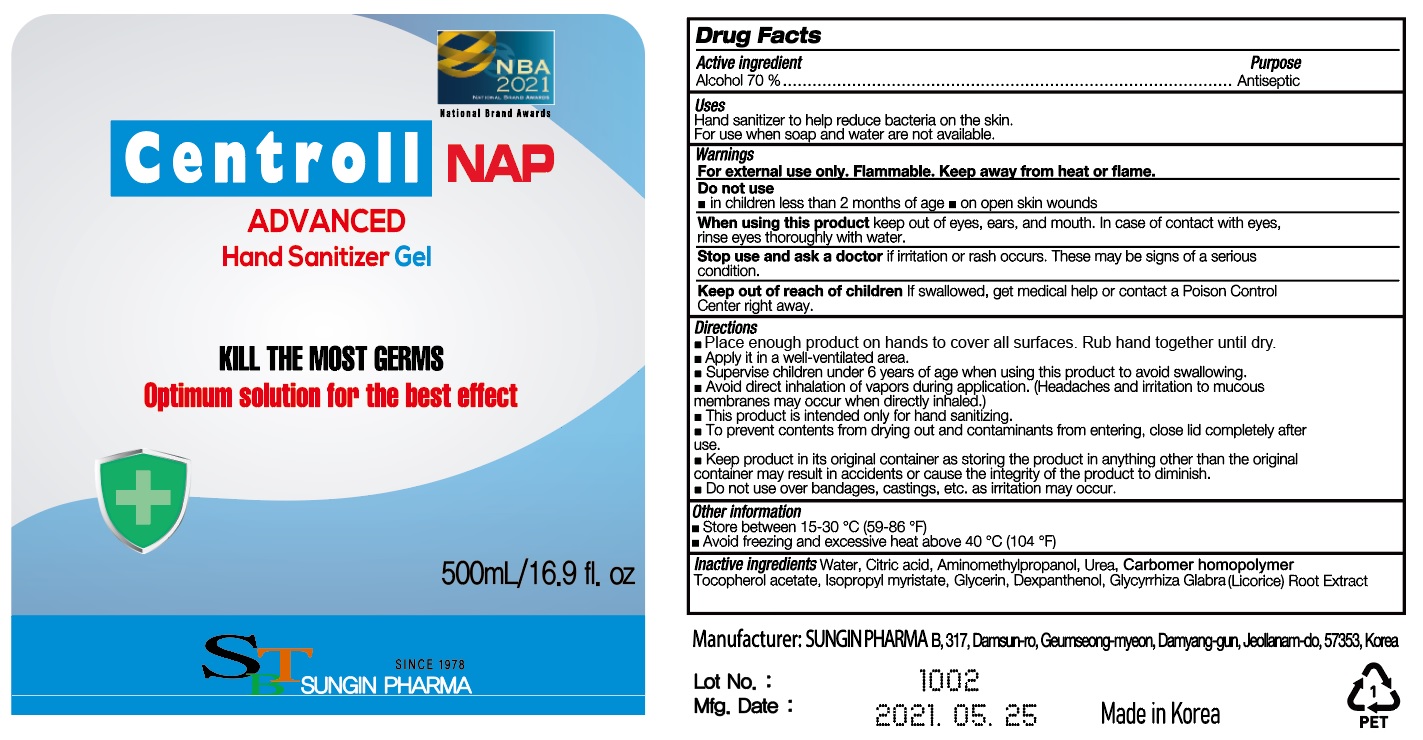 DRUG LABEL: Centroll NAP ADVANCED Hand Sanitizer Gel
NDC: 82037-510 | Form: GEL
Manufacturer: SUNGIN PHARMA
Category: otc | Type: HUMAN OTC DRUG LABEL
Date: 20210721

ACTIVE INGREDIENTS: ALCOHOL 350 mL/500 mL
INACTIVE INGREDIENTS: CARBOMER HOMOPOLYMER, UNSPECIFIED TYPE; CITRIC ACID MONOHYDRATE; GLYCERIN; GLYCYRRHIZA GLABRA; WATER; AMINOMETHYLPROPANOL; .ALPHA.-TOCOPHEROL ACETATE; UREA; DEXPANTHENOL; ISOPROPYL MYRISTATE

[82037-510-01] [Gel] [Bottle+Pump] [500 mL] Centroll NAP ADVANCED Hand Sanitizer Gel

Active ingredient

Alcohol 70 %

Purpose

Antiseptic

Uses

Hand sanitizer to help reduce bacteria on the skin.

For use when soap and water are not available.

Warnings

For external use only. Flammable. Keep away from heat or flame.

Do not use

■ in children less than 2 months of age ■ on open skin wounds

When using this product

keep out of eyes, ears, and mouth. In case of contact with eyes, rinse eyes thoroughly with water.

Stop use and ask a doctor

if irritation or rash occurs. These may be signs of a serious condition.

Keep out of reach of children

If swallowed, get medical help or contact a Poison Control Center right away.

Directions

■ Place enough product on hands to cover all surfaces. Rub hand together until dry.

■ Apply it in a well-ventilated area.

■ Supervise children under 6 years of age when using this product to avoid swallowing.

■ Avoid direct inhalation of vapors during application. (Headaches and irritation to mucous membranes may occur when directly inhaled.)

■ This product is intended only for hand sanitizing.

■ To prevent contents from drying out and contaminants from entering, close lid completely after use.

■ Keep product in its original container as storing the product in anything other than the original container may result in accidents or cause the integrity of the product to diminish.

■ Do not use over bandages, castings, etc. as irritation may occur.

Other information

■ Store between 15-30 °C (59-86 °F)

■ Avoid freezing and excessive heat above 40 °C (104 °F)

Inactive ingredients

Water, Citric acid, Aminomethylpropanol, Urea, Carbomer homopolymer,Tocopherol acetate, Isopropyl myristate, Glycerin, Dexpanthenol, Glycyrrhiza Glabra (Licorice) Root Extract